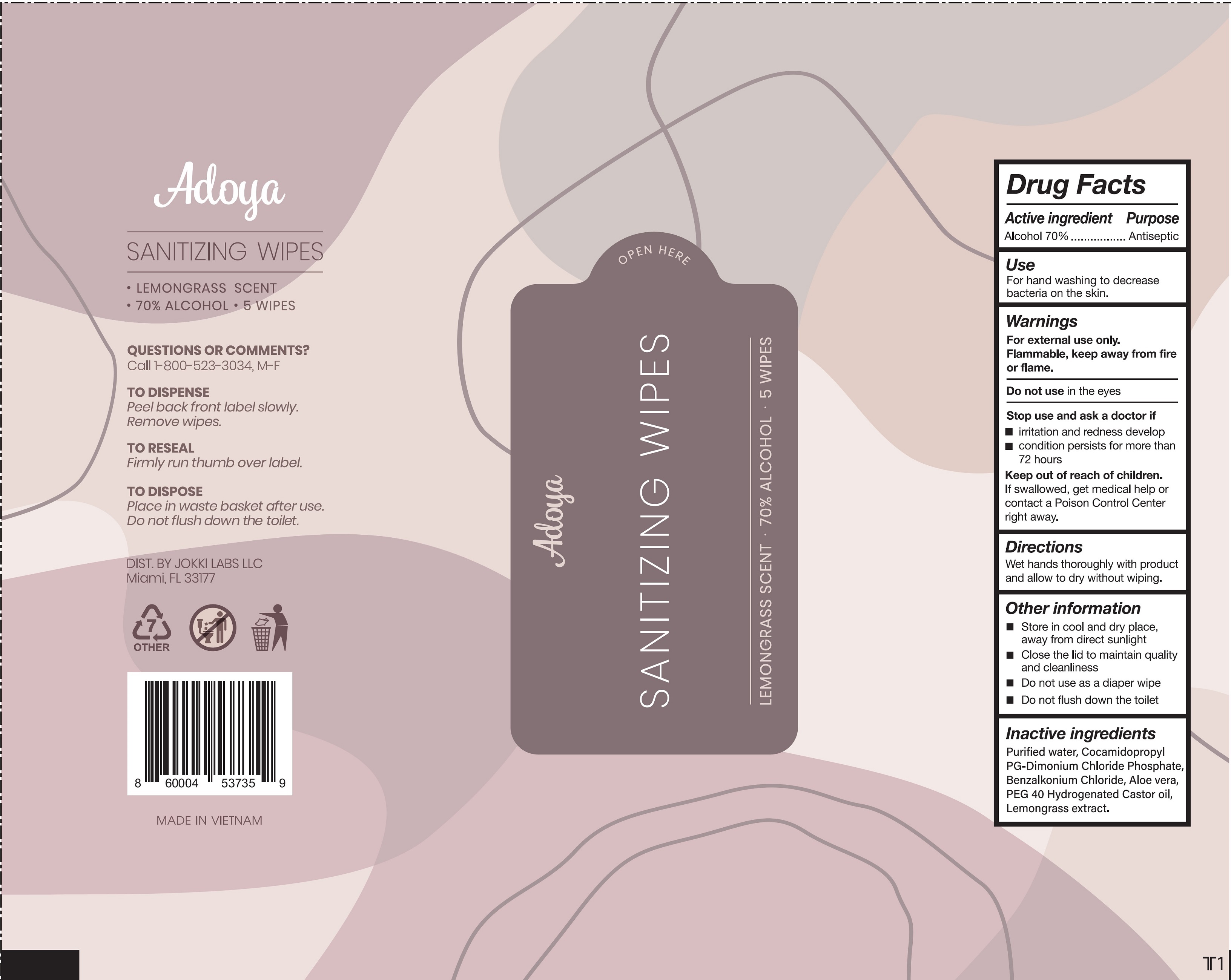 DRUG LABEL: Adoya Sanitizing Wipes Lemongrass Scent
NDC: 79708-002 | Form: CLOTH
Manufacturer: Jokki Labs LLC
Category: otc | Type: HUMAN OTC DRUG LABEL
Date: 20201112

ACTIVE INGREDIENTS: ALCOHOL 0.7 mL/1 mL
INACTIVE INGREDIENTS: WATER; COCAMIDOPROPYL PG-DIMONIUM CHLORIDE PHOSPHATE; BENZALKONIUM CHLORIDE; ALOE VERA LEAF; CYMBOPOGON CITRATUS LEAF

Adoya Sanitizing Wipes Lemongrass Scent

Active ingredient

Alcohol 70%

Purpose

Antiseptic

Use

For hand washing to decrease bacteria on the skin.

Warnings

For external use only.

Flammable, keep away from fire or flame.

Do not use

in the eyes

Stop use and ask a doctor if

- irritation or redness develop
- condition persists for more than 72 hours

Keep out of reach of children.

If swallowed, get medical help or contact a Poison Control Center right away.

Directions

Wet hands thoroughly with product and allow to dry without wiping.

Other information

- Store in cool and dry place, away from direct sunlight
- Close the lid to maintain quality and cleanliness
- Do not use as a diaper wipe
- Do not flush down the toilet

Inactive ingredients

Purified water, Cocamidopropyl PG-Dimonium Chloride Phosphate, Benzalkonium Chloride, Aloe vera, PEG 40 Hydrogenated Castor oil, Lemongrass extract.